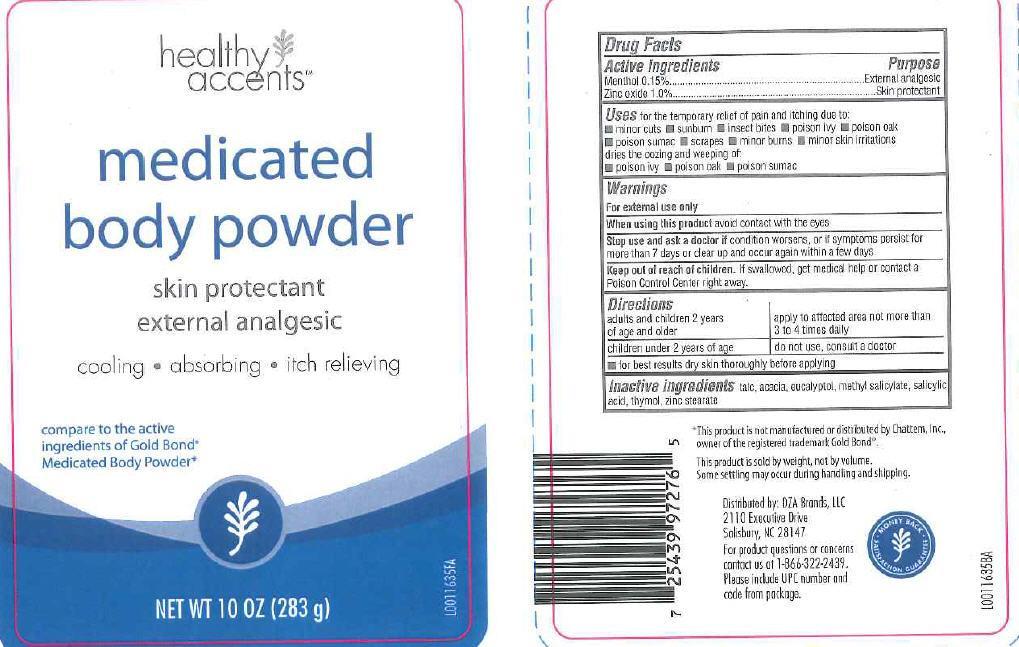 DRUG LABEL: Medicated
NDC: 55316-551 | Form: POWDER
Manufacturer: DZB Brands, LLC
Category: otc | Type: HUMAN OTC DRUG LABEL
Date: 20130121

ACTIVE INGREDIENTS: MENTHOL 1.5 mg/1 g; ZINC OXIDE 10 mg/1 g
INACTIVE INGREDIENTS: TALC; ACACIA; EUCALYPTOL; METHYL SALICYLATE; SALICYLIC ACID; THYMOL; ZINC STEARATE

Drug Facts

Active ingredients

Menthol 0.15%

Zinc oxide 1.0%

Purpose

External analgesic

Skin protectant

Uses

Uses for the temporary relief of pain and itching due to:

- minor cuts
- sunburn
- insect bites
- poison ivy
- poison oak
- poison sumac
- scrapes
- minor burns
- minor skin irritations

dries the oozing and weeping of:

- poison ivy
- poison oak
- poison sumac

Warnings

For external use only

When using this product avoid contact with the eyes

Stop use

Stop use and ask a doctor if condition worsens, or if symptoms persist for more than 7 days or clear up and occur again within a few days

Keep out of reach of children. If swallowed, get medical help or contact a Poison Control Center right away.

Directions

adults and children 2 years of age and older - apply to affected area not more than 3 to 4 times daily

children under 2 years of age - do not use, consult a doctor

- for best results dry skin thoroughly before applying

Inactive ingredients

Inactive ingredients talc, acacia, eucalyptol, methyl salicylate, salicylic acid, thymol, zinc stearate

Disclaimer

This product is not manufractured or distributed by Chattem, Inc., owner of the registered tradmark Gold Bond

This product is sold by weight, not by volume. Some settling may occur during handling and shipping

Advese reactions

Distributed by: DZA Brands, LLC

2110 Excutive Drive

Salisbury, NC 28147

For Product questions or concerns

contact us at 1-866-322-2439. Please include UPC number and code from package

Principal Display Panel

Healthy

Accents

medicated

body powder

external analgesic

cooling - absorbing- itch relieving

Compare to the active ingredients of Gold Bond Medicated Body Powder

NET WT 10 OZ (283 g)